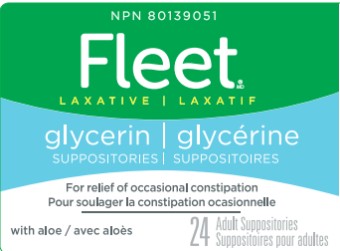 DRUG LABEL: FLEET
NDC: 0132-0090 | Form: SUPPOSITORY
Manufacturer: C.B. Fleet Company, Inc.
Category: otc | Type: HUMAN OTC DRUG LABEL
Date: 20251030

ACTIVE INGREDIENTS: GLYCERIN 2 g/1 1
INACTIVE INGREDIENTS: ALOE; EDETATE DISODIUM; WATER; SODIUM HYDROXIDE; STEARIC ACID

Fleet Glycerin Suppository_0132-0090

Drug Facts

Active ingredient (in each suppository)

Glycerin 2g

Purpose

Hyperosmotic laxative

Uses

- for relief of occasional constipation
- this product usually produces bowel movement in ¼ to 1 hour

Warnings

For rectal use only.

Do not use

laxative products when abdominal pain, nausea, or vomiting are present unless directed by a doctor.

Ask a doctor before using any laxative if you

- have a sudden change in bowel habits lasting more than 2 weeks
- already used a laxative for more than 1 week

When using this product

rectal discomfort or burning sensation may occur.

Stop using this product and consult a doctor if you have

- rectal bleeding

- no bowel movement within 1 hour of using this product

These symptoms may indicate a serious condition.

Keep out of reach of children.

If swallowed, get medical help or contact a Poison Control Center right away.

Directions

Single Daily Dosage (per 24 hours)

adults and children 6 years and over | 1 suppository or as directed by a doctor
children 2 to under 6 years | use Fleet® Pedia-Lax®™ Suppositories
children under 2 years | consult a doctor

Insert suppository well up into rectum, to produce laxative action. Suppository is designed to dissolve only partially, which may not be noticeable.

Other information

- Store container tightly closed.
- Keep away from excessive heat.
- Mouth of jar sealed for safety. If foil imprinted with green Fleet® emblem is missing or torn, do not use.

Inactive ingredients

aloe vera leaf, edetate disodium, purified water, sodium hydroxide, stearic acid

Questions?

1-866-255-6960 or www.fleetlabs.com

Principal Display Panel

Fleet®
Glycerin
Laxative suppositories
24 adult suppositories